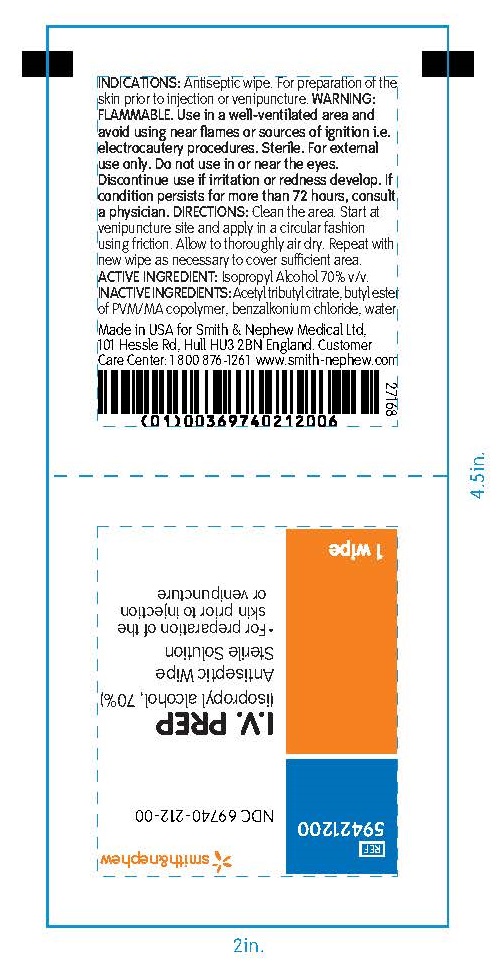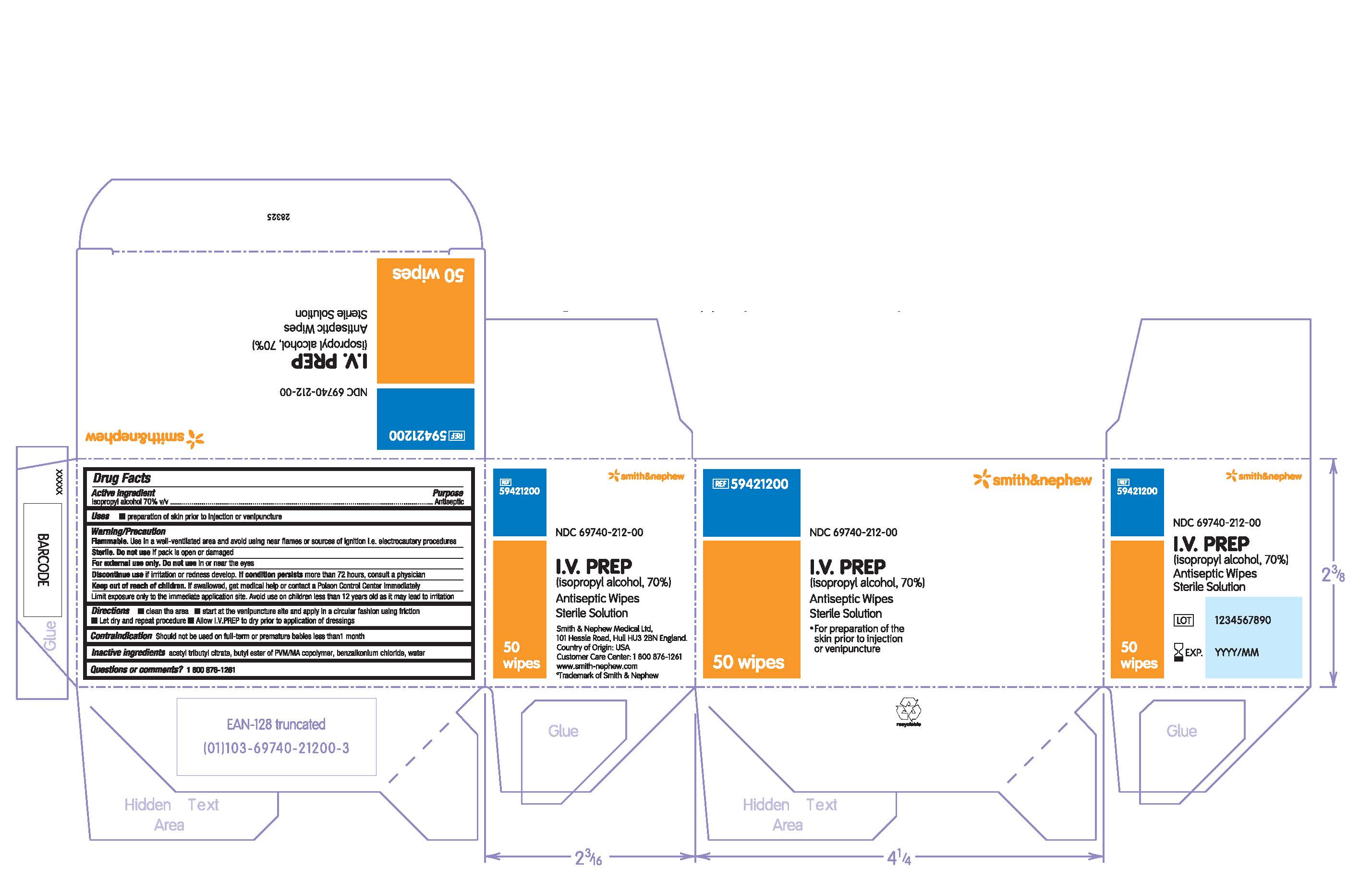 DRUG LABEL: I.V. Prep Antiseptic Wipe
NDC: 69740-212 | Form: CLOTH
Manufacturer: Smith & Nephew, Medical Ltd
Category: otc | Type: HUMAN OTC DRUG LABEL
Date: 20240321

ACTIVE INGREDIENTS: ISOPROPYL ALCOHOL 70 mL/100 mL
INACTIVE INGREDIENTS: ACETYLTRIBUTYL CITRATE; WATER; BENZALKONIUM CHLORIDE

I.V. Prep Antiseptic Wipe
Sterile Solution

ACTIVE INGREDIENTS (IN EACH PACKET)

Isopropyl Alcohol 70% v/v

PURPOSE

Antiseptic

USES

For preparation of skin prior to injection or venipuncture

WARNINGS

- FLAMMABLEUse in a well-ventilated area and avoid using near flames or sources of ignition i.e. electrocautery procedures
- Sterile. Do not useif pack is open or damaged
- For external use only. Do not usein or near the eyes
- Discontinue useif irritation or redness develop. If condition persistsmore than 72 hours, consult a physician
- Limit exposure only to the immediate application site. Avoid use on children less than 12 years old as it may lead to irritation

Keep out of reach of children. If swallowed, get medical help or contact a Poisin Control Center immediately

DIRECTIONS

- clean the area
- start at the venipuncture site and apply in a circular fashion using friction
- Let dry and repeat procedure
- Allow I.V. PREP to dry prior to application of dressings

CONTRAINDICATION

Should not be used on full-term or premature babies less than 1 month

INACTIVE INGREDIENTS

acetyl tributyl citrate, butyl ester of PVM/MA copolymer, benzalkonium chloride, water

QUESTIONS

Made in the USA for Smith & Nephew Medical Ltd

101 Hessle Road, Hull, HU3 2BN, England

Customer Care Center: 1 800 876-1261

www.smith-nephew.com

PACKAGE LABEL

PACKAGE LABEL - PRINCIPAL DISPLAY PANEL- BOX OF 50 WIPES (Front)

#59421200

NDC 69740-212-00

I.V. PREP

(isopropyl alcohol, 70%)

Antiseptic Wipes

Sterile Solution

- For preparation of the skin prior to injection or venipuncture

50 Wipes

PACKAGE LABEL - PRINCIPAL DISPLAY PANEL- 1 Packet

#59421200

NDC 69740-212-00

I.V. PREP

(isopropyl alcohol, 70%)

Antiseptic Wipe

Sterile Solution

- For preparation of the skin prior to injection or venipuncture

1 Wipe

Made in the USA for Smith & Nephew Medical Ltd

101 Hessle Road, Hull, HU3 2BN, England

Customer Care Center: 1 800 876-1261

www.smith-nephew.com